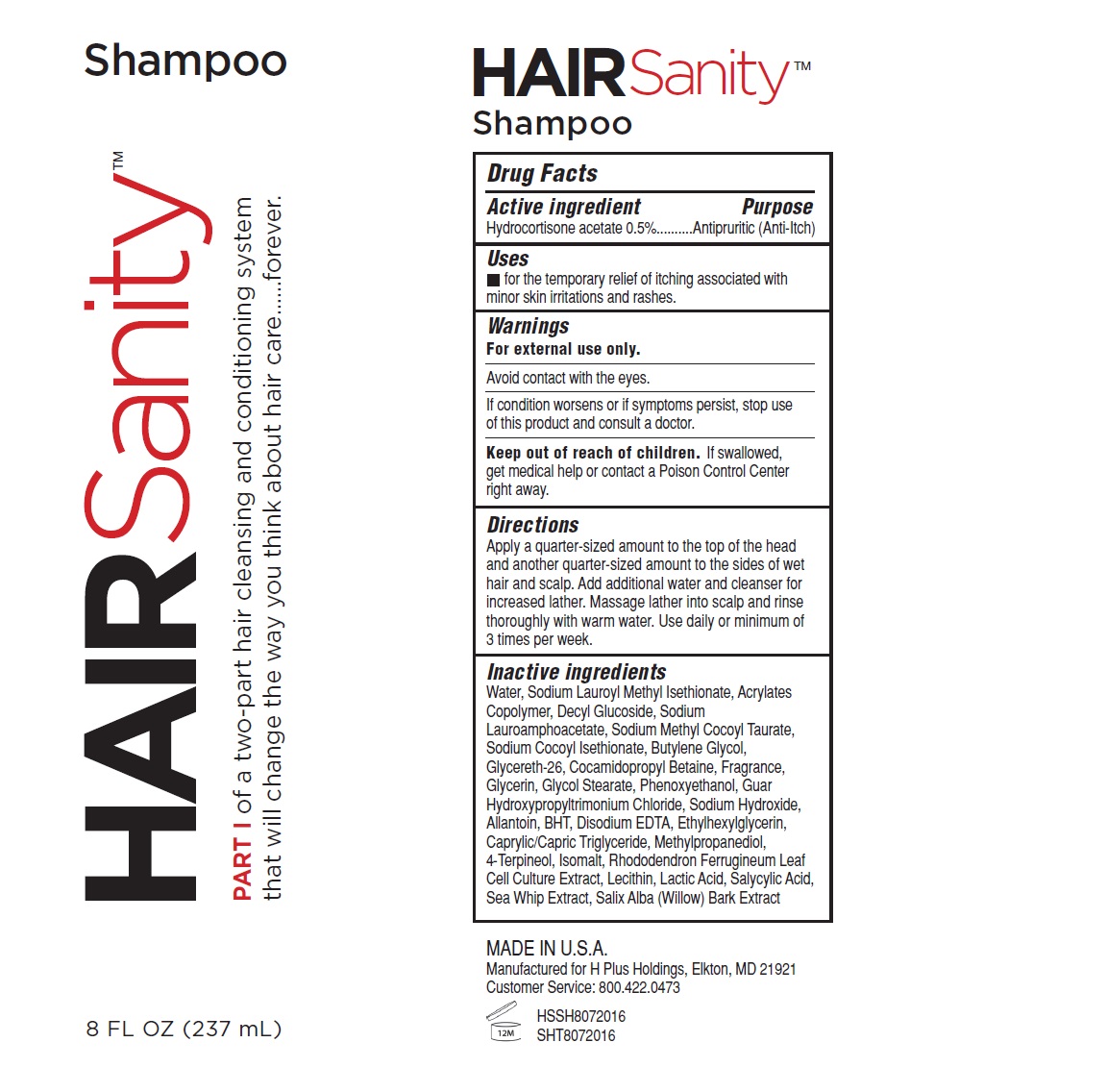 DRUG LABEL: Hair Sanity
NDC: 58443-0246 | Form: LOTION/SHAMPOO
Manufacturer: Prime Enterprises Inc.
Category: otc | Type: HUMAN OTC DRUG LABEL
Date: 20200117

ACTIVE INGREDIENTS: HYDROCORTISONE ACETATE 5 mg/1 mL
INACTIVE INGREDIENTS: PHENOXYETHANOL; ETHYLHEXYLGLYCERIN; SODIUM COCOYL ISETHIONATE; SODIUM HYDROXIDE; SODIUM LAUROAMPHOACETATE; SODIUM LAUROYL METHYL ISETHIONATE; SODIUM METHYL COCOYL TAURATE; COCAMIDOPROPYL BETAINE; SALICYLIC ACID; SALIX ALBA BARK; METHACRYLIC ACID - ETHYL ACRYLATE COPOLYMER (4500 MPA.S); ALLANTOIN; BUTYLATED HYDROXYTOLUENE; BUTYLENE GLYCOL; MEDIUM-CHAIN TRIGLYCERIDES; CAPRYLYL GLYCOL; PSEUDOPTEROGORGIA ELISABETHAE; DECYL GLUCOSIDE; EDETATE DISODIUM; GLYCERETH-26; GLYCERIN; GLYCOL STEARATE; GUAR HYDROXYPROPYLTRIMONIUM CHLORIDE (1.7 SUBSTITUENTS PER SACCHARIDE); ISOMALT; RHODODENDRON FERRUGINEUM LEAF; METHYLPROPANEDIOL; 4-TERPINEOL, (+)-; WATER

Hair Sanity Part I

Active Ingredients

Hydrocortisone acetate 0.5%

Purpose

Antipruritic (Anti-Itch)

Uses

- for the temporary relief of itching associated with minor skin irritations and rashes.

Warnings

For external use only.

WHEN USING

Avoid contact with the eyes.

ASK DOCTOR

If conditions worsens or if symptoms persist, stop use of this product and consult a doctor.

Keep out of reach of children. If swallowed, get medical help or contact a Poison Control Center right away.

Directions

Apply a quarter-sized amount to the top of the head and another quarter-sized amount to the sides of wet hair and scalp. Add additional water and cleanser for increased lather. Massage lather into scalp and rinse thoroughly with warm water. Use daily or minimum of 3 times per week.

INACTIVE INGREDIENT

Water, Sodium Lauroyl Methyl Isethionate, Acrylates Copolymer, Decyl Glucoside, Sodium Lauroamphoacetate, Sodium Methyl Cocoyl Taurate, Sodium Cocoyl Isethionate, Butylene Glycol, Glycereth-26, Cocamidopropyl Betaine, Fragrance, Glycerin, Glycol Stearate, Phenoxyethanol, Guar Hydroxypropyltrimonium Chloride, Sodium Hydroxide, Allantoin, BHT, Disodium EDTA, Ethylhexylglycerin, Caprylic/Capric Triglyceride, Methylpropanediol, 4-Terpineol, Isomalt, Rhododendron Ferrugineum Leaf Cell Culture Extract, Lecithin, Lactic Acid, Salicylic Acid, Sea Whip Extract, Salix Alba (Willow) Bark Extract